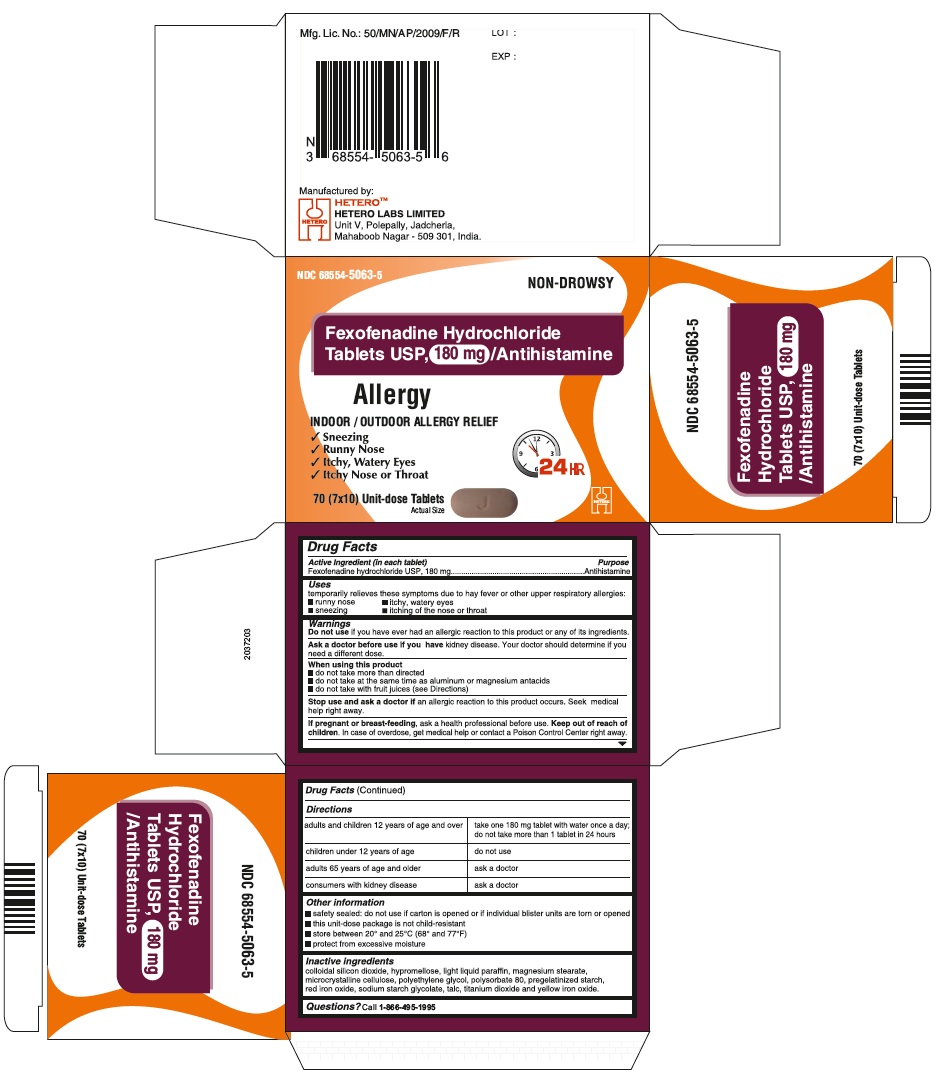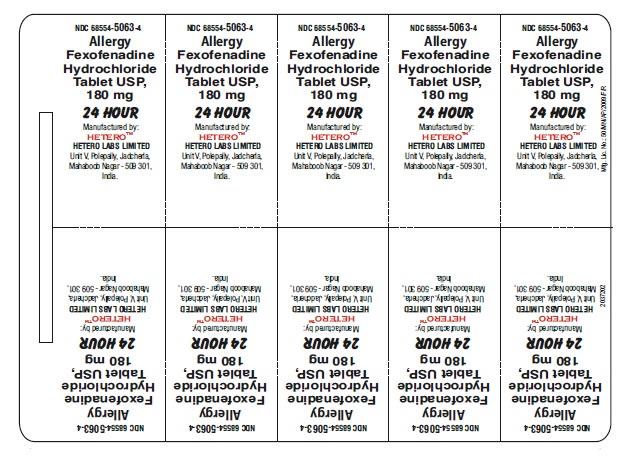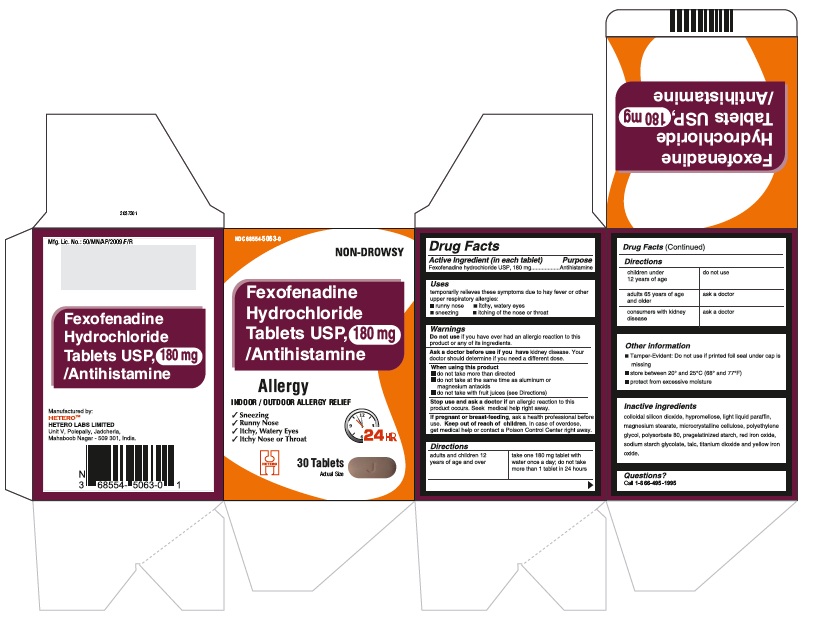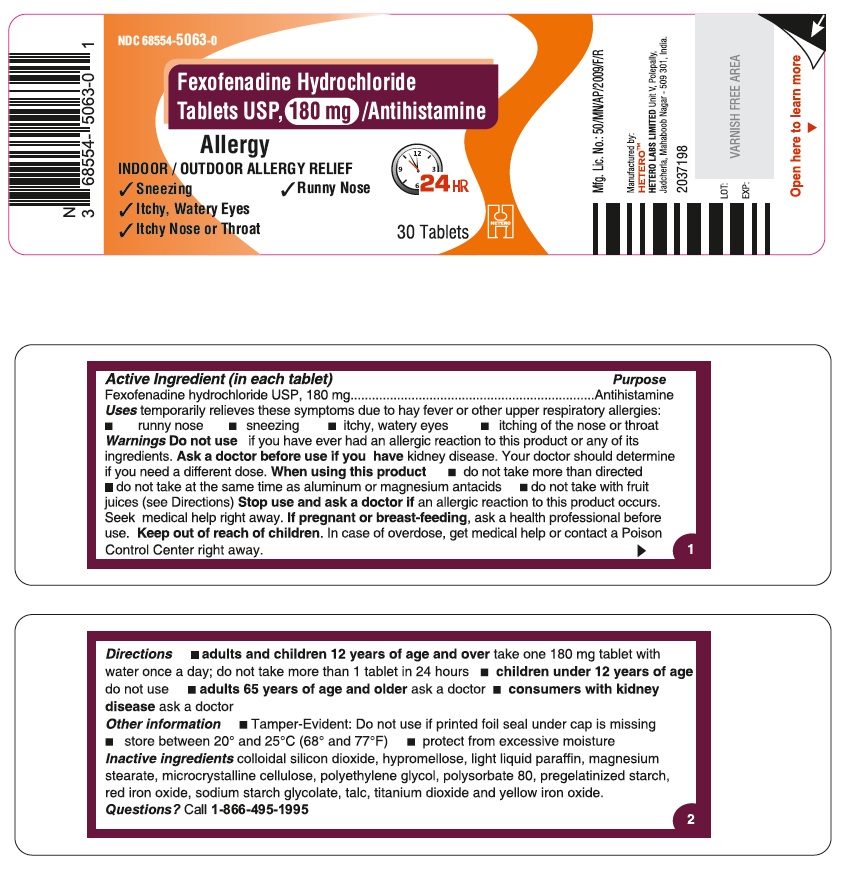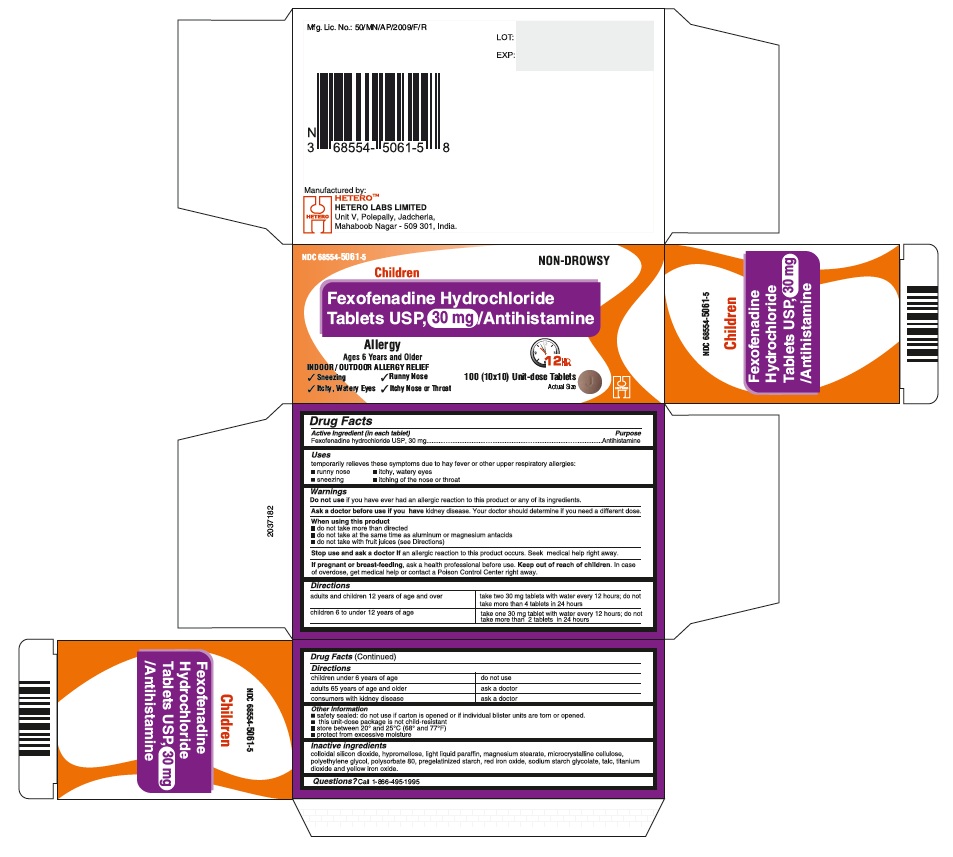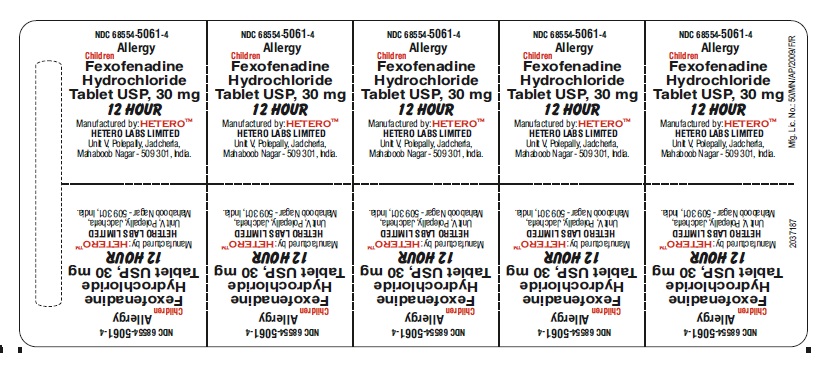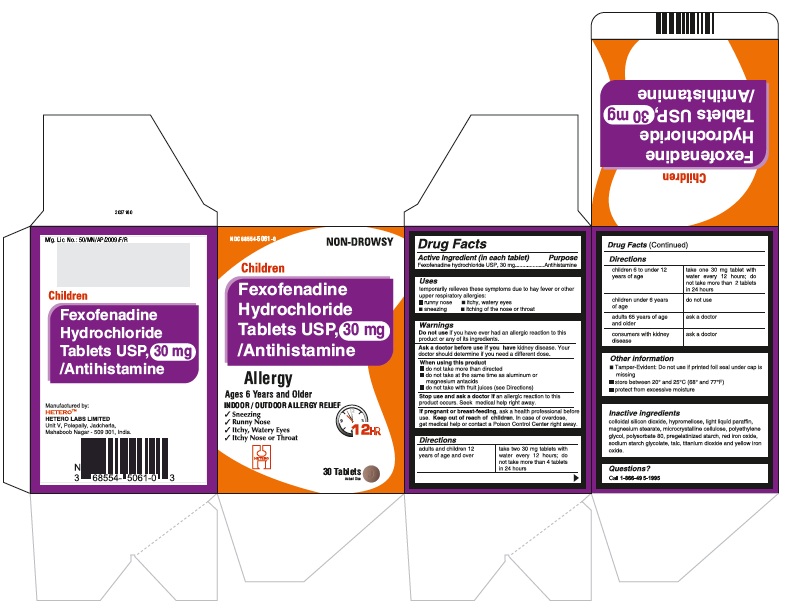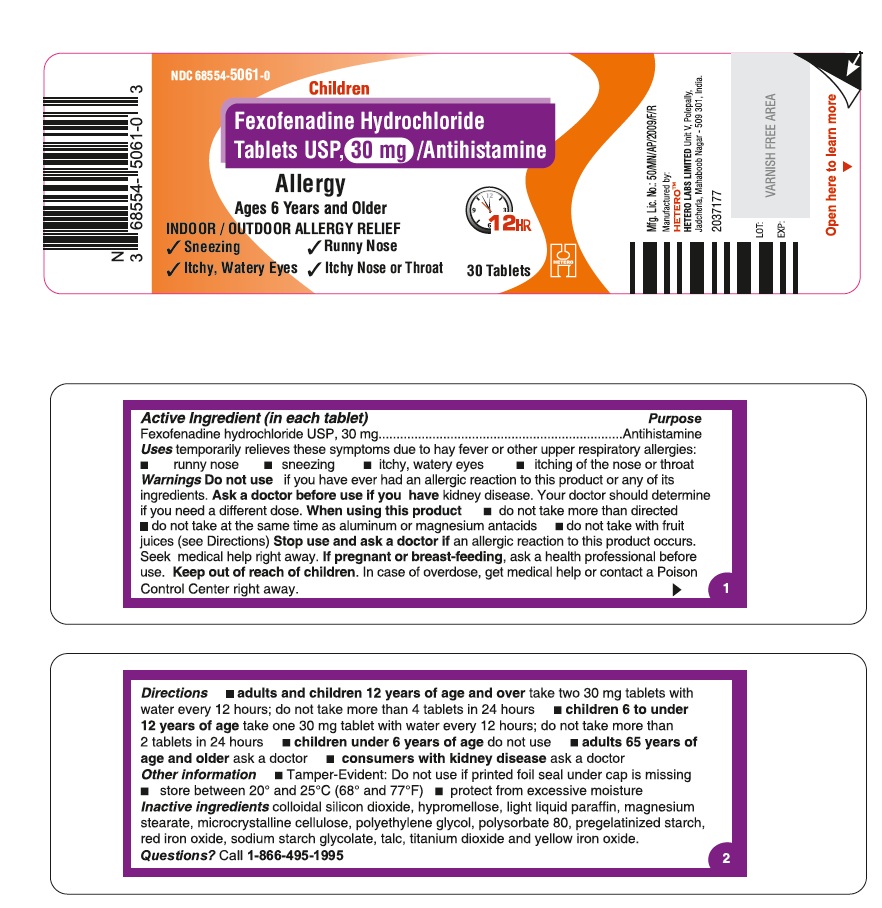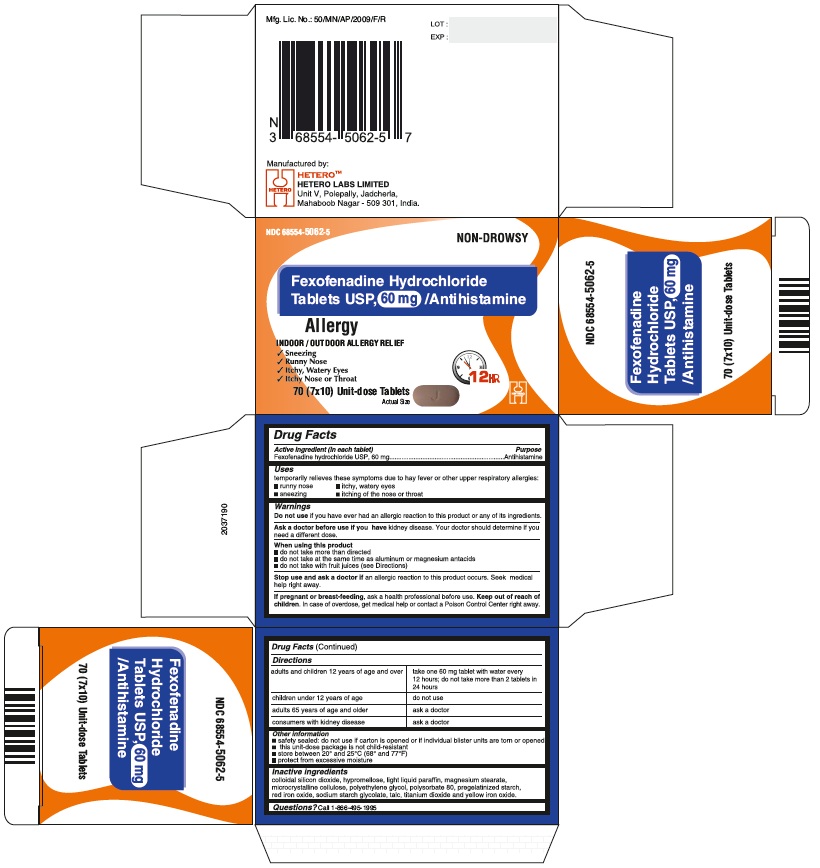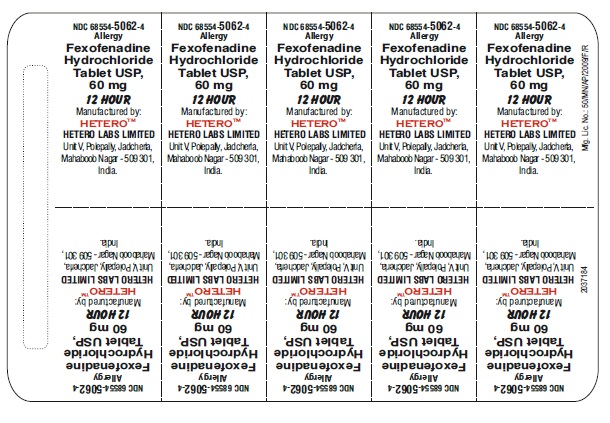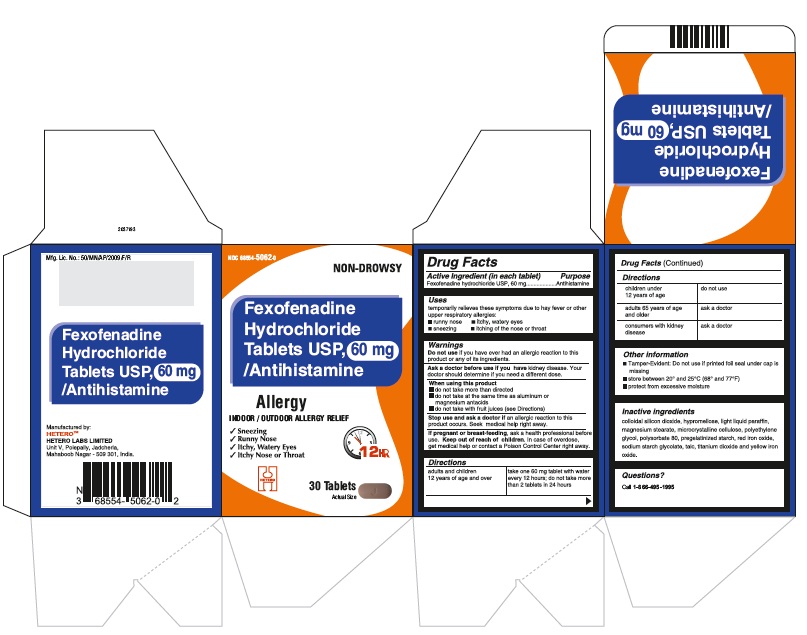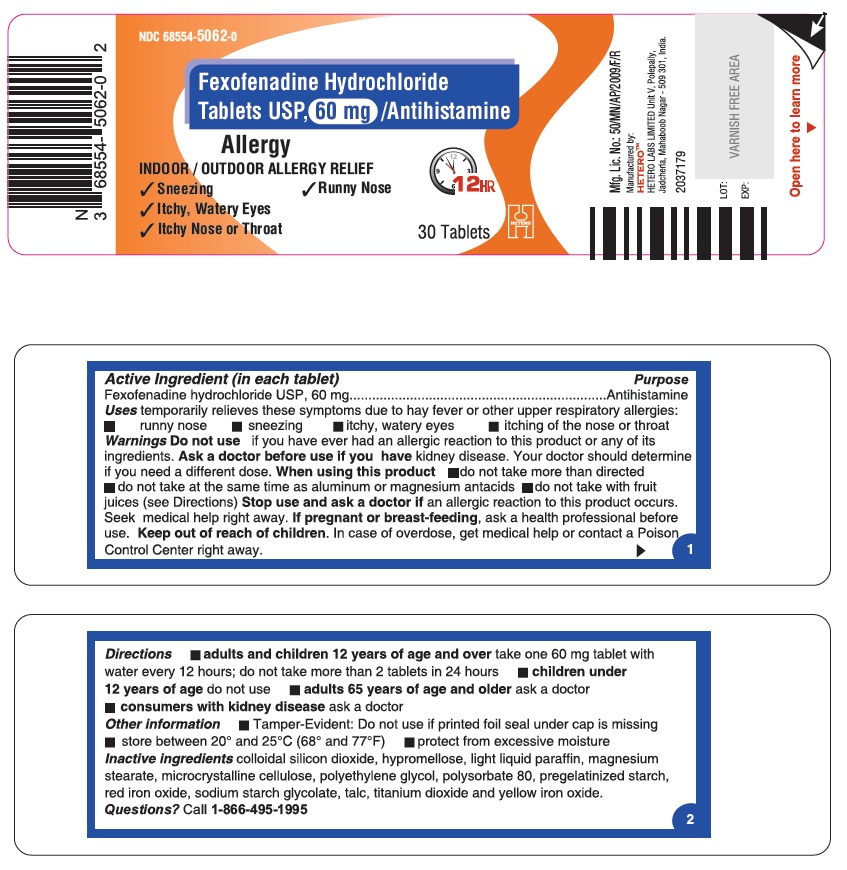 DRUG LABEL: Fexofenadine Hydrochloride
NDC: 68554-5061 | Form: TABLET, FILM COATED
Manufacturer: Hetero Labs Limited
Category: otc | Type: Human OTC Drug Label
Date: 20160908

ACTIVE INGREDIENTS: FEXOFENADINE HYDROCHLORIDE 30 mg/1 1
INACTIVE INGREDIENTS: SILICON DIOXIDE; MAGNESIUM STEARATE; CELLULOSE, MICROCRYSTALLINE; STARCH, CORN; SODIUM STARCH GLYCOLATE TYPE A POTATO; HYPROMELLOSES; LIGHT MINERAL OIL; POLYETHYLENE GLYCOLS; POLYSORBATE 80; FERRIC OXIDE RED; TALC; TITANIUM DIOXIDE; FERRIC OXIDE YELLOW

Fexofenadine Hydrochloride Tablets USP, 30 mg, 60 mg and 180 mg

ACTIVE INGREDIENT(S)

(in each tablet)
Fexofenadine Hydrochloride USP, 30 mg
Fexofenadine Hydrochloride USP, 60 mg
Fexofenadine Hydrochloride USP, 180 mg

PURPOSE

Antihistamine

USE(S)

temporarily relieves these symptoms due to hay fever or other upper respiratory allergies:

- runny nose
- sneezing
- itchy, watery eyes
- itching of the nose or throat

DO NOT USE

if you have ever had an allergic reaction to this product or any of its ingredients.

ASK A DOCTOR BEFORE USE IF

you have kidney disease. Your doctor should determine if you need a different dose.

WHEN USING THIS PRODUCT

- do not take more than directed
- do not take at the same time as aluminum or magnesium antacids
- do not take with fruit juices (see Directions)

STOP USE AND ASK DOCTOR IF

an allergic reaction to this product occurs. Seek medical help right away.

PREGNANCY/BREASTFEEDING

ask a health professional before use.

KEEP OUT OF REACH OF CHILDREN

In case of overdose, get medical help or contact a Poison Control Center right away.

DIRECTIONS

30 mg

adults and children 12 years of age and over | take two 30 mg tablets with water every 12 hours; do not take more than 4 tablets in 24 hours
children 6 to under 12 years of age | take one 30 mg tablet with water every 12 hours; do not take more than 2 tablets in 24 hours
children under 6 years of age | do not use
adults 65 years of age and older | ask a doctor
consumers with kidney disease | ask a doctor

60 mg

adults and children 12 years of age and over | take one 60 mg tablet with water every 12 hours; do not take more than 2 tablets in 24 hours
children under 12 years of age | do not use
adults 65 years of age and older | ask a doctor
consumers with kidney disease | ask a doctor

180 mg

adults and children 12 years of age and over | take one 180 mg tablet with water once a day; do not take more than 1 tablet in 24 hours
children under 12 years of age | do not use
adults 65 years of age and older | ask a doctor
consumers with kidney disease | ask a doctor

OTHER INFORMATION

- Tamper Evident: Do not use if printed foil seal under cap is missing
- This unit-dose package is not child-resistant
- store between 20º and 25ºC (68º and 77ºF)
- protect from excessive moisture

INACTIVE INGREDIENTS

Colloidal silicon dioxide, hypromellose, light liquid paraffin, magnesium stearate, microcrystalline cellulose, polyethylene glycol, polysorbate 80, pregelatinized starch, red iron oxide, sodium starch glycolate, talc, titanium dioxide and yellow iron oxide.

QUESTIONS?

Call 1-866-495-1995

PRINCIPAL DISPLAY PANEL

Fexofenadine Hydrochloride Tablets USP, 30 mg - Container Carton

Fexofenadine Hydrochloride Tablets USP, 30 mg - Container Label

Fexofenadine Hydrochloride Tablets USP, 30 mg - Blister Foil

Fexofenadine Hydrochloride Tablets USP, 30 mg - Blister Carton

Fexofenadine Hydrochloride Tablets USP, 60 mg - Container Carton

Fexofenadine Hydrochloride Tablets USP, 60 mg - Container Label

Fexofenadine Hydrochloride Tablets USP, 60 mg - Blister Foil

Fexofenadine Hydrochloride Tablets USP, 60 mg - Blister Carton

Fexofenadine Hydrochloride Tablets USP, 180 mg - Container Carton

Fexofenadine Hydrochloride Tablets USP, 180 mg - Container Label

Fexofenadine Hydrochloride Tablets USP, 180 mg - Blister Foil

Fexofenadine Hydrochloride Tablets USP, 180 mg - Blister Carton